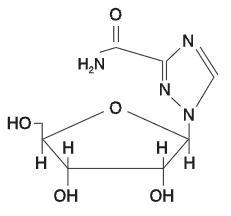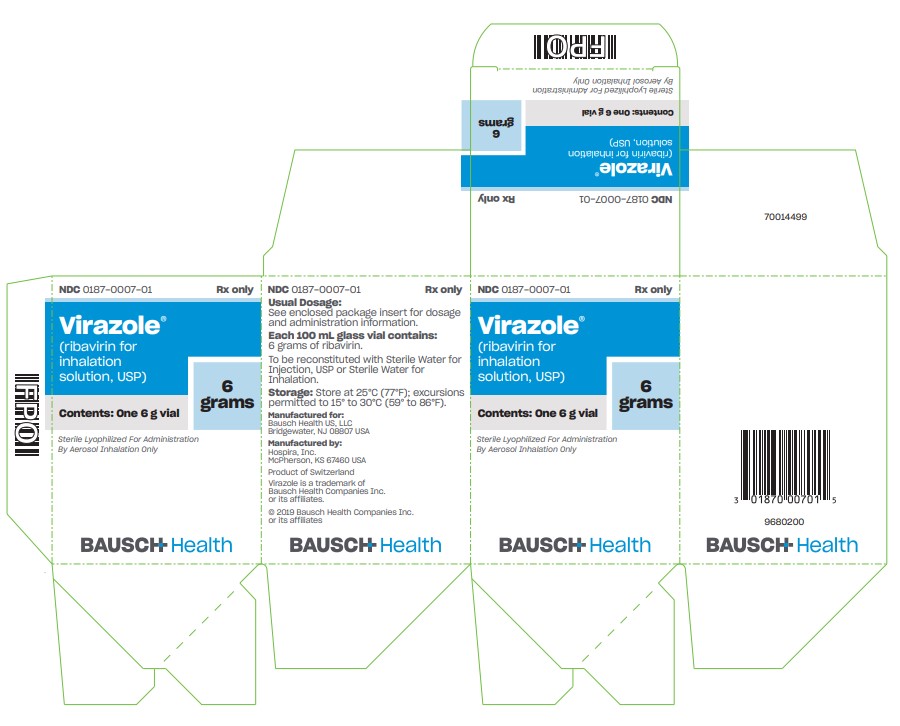 DRUG LABEL: Virazole
NDC: 0187-0007 | Form: POWDER, FOR SOLUTION
Manufacturer: Bausch Health US, LLC
Category: prescription | Type: HUMAN PRESCRIPTION DRUG LABEL
Date: 20250814

ACTIVE INGREDIENTS: Ribavirin 6 g/1 1

VIRAZOLE®
(Ribavirin for Inhalation Solution, USP)

PRESCRIBING INFORMATION

WARNINGS

USE OF AEROSOLIZED VIRAZOLE IN PATIENTS REQUIRING MECHANICAL VENTILATOR ASSISTANCE SHOULD BE UNDERTAKEN ONLY BY PHYSICIANS AND SUPPORT STAFF FAMILIAR WITH THE SPECIFIC VENTILATOR BEING USED AND THIS MODE OF ADMINISTRATION OF THE DRUG. STRICT ATTENTION MUST BE PAID TO PROCEDURES THAT HAVE BEEN SHOWN TO MINIMIZE THE ACCUMULATION OF DRUG PRECIPITATE, WHICH CAN RESULT IN MECHANICAL VENTILATOR DYSFUNCTION AND ASSOCIATED INCREASED PULMONARY PRESSURES (SEE WARNINGS).

SUDDEN DETERIORATION OF RESPIRATORY FUNCTION HAS BEEN ASSOCIATED WITH INITIATION OF AEROSOLIZED VIRAZOLE USE IN INFANTS. RESPIRATORY FUNCTION SHOULD BE CAREFULLY MONITORED DURING TREATMENT. IF INITIATION OF AEROSOLIZED VIRAZOLE TREATMENT APPEARS TO PRODUCE SUDDEN DETERIORATION OF RESPIRATORY FUNCTION, TREATMENT SHOULD BE STOPPED AND REINSTITUTED ONLY WITH EXTREME CAUTION, CONTINUOUS MONITORING AND CONSIDERATION OF CONCOMITANT ADMINISTRATION OF BRONCHODILATORS (SEE WARNINGS).

VIRAZOLE IS NOT INDICATED FOR USE IN ADULTS. PHYSICIANS AND PATIENTS SHOULD BE AWARE THAT RIBAVIRIN HAS BEEN SHOWN TO PRODUCE TESTICULAR LESIONS IN RODENTS AND TO BE TERATOGENIC IN ALL ANIMAL SPECIES IN WHICH ADEQUATE STUDIES HAVE BEEN CONDUCTED (RODENTS AND RABBITS) (SEE CONTRAINDICATIONS).

DESCRIPTION

VIRAZOLE® (Ribavirin for Inhalation Solution, USP) is a brand name for ribavirin, a synthetic nucleoside with antiviral activity. VIRAZOLE for inhalation solution is a sterile, lyophilized powder to be reconstituted for aerosol administration. Each 100 mL glass vial contains 6 grams of ribavirin, and when reconstituted to the recommended volume of 300 mL with Sterile Water for Injection, USP or Sterile Water for Inhalation (no preservatives added), will contain 20 mg of ribavirin per mL, pH approximately 5.5. Aerosolization is to be carried out in a Small Particle Aerosol Generator (SPAG®-2) nebulizer only.

Ribavirin is 1-beta-D-ribofuranosyl-1H-1,2,4-triazole-3-carboxamide, with the following structural formula:

Ribavirin is a stable, white crystalline compound with a maximum solubility in water of 142 mg/mL at 25°C and with only a slight solubility in ethanol. The empirical formula is C8H12N4O5 and the molecular weight is 244.21.

CLINICAL PHARMACOLOGY

Mechanism of Action

In cell cultures the inhibitory activity of ribavirin for respiratory syncytial virus (RSV) is selective. The mechanism of action is unknown. Reversal of the in vitro antiviral activity by guanosine or xanthosine suggests ribavirin may act as an analogue of these cellular metabolites.

Microbiology

Ribavirin has demonstrated antiviral activity against RSV in vitro^1 and in experimentally infected cotton rats.^2 Several clinical isolates of RSV were evaluated for ribavirin susceptibility by plaque reduction in tissue culture. Plaques were reduced 85-98% by 16 mcg/mL; however, results may vary with the test system. The development of resistance has not been evaluated in vitro or in clinical trials.

In addition to the above, ribavirin has been shown to have in vitro activity against influenza A and B viruses and herpes simplex virus, but the clinical significance of these data is unknown.

Immunologic Effects

Neutralizing antibody responses to RSV were decreased in aerosolized VIRAZOLE-treated infants compared to placebo-treated infants.^3 One study also showed that RSV-specific IgE antibody in bronchial secretions was decreased in patients treated with aerosolized VIRAZOLE. In rats, ribavirin administration resulted in lymphoid atrophy of the thymus, spleen and lymph nodes. Humoral immunity was reduced in guinea pigs and ferrets. Cellular immunity was also mildly depressed in animal studies. The clinical significance of these observations is unknown.

Pharmacokinetics

Assay for VIRAZOLE in human materials is by a radioimmunoassay which detects ribavirin and at least one metabolite.

VIRAZOLE brand of ribavirin, when administered by aerosol, is absorbed systemically. Four pediatric patients inhaling VIRAZOLE aerosol administered by face mask for 2.5 hours each day for 3 days had plasma concentrations ranging from 0.44 to 1.55 µM, with a mean concentration of 0.76 µM. The plasma half-life was reported to be 9.5 hours. Three pediatric patients inhaling aerosolized VIRAZOLE administered by face mask or mist tent for 20 hours each day for 5 days had plasma concentrations ranging from 1.5 to 14.3 µM, with a mean concentration of 6.8 µM.

The bioavailability of aerosolized VIRAZOLE is unknown and may depend on the mode of aerosol delivery. After aerosol treatment, peak plasma concentrations of ribavirin are 85% to 98% less than the concentration that reduced RSV plaque formation in tissue culture. After aerosol treatment, respiratory tract secretions are likely to contain ribavirin in concentrations manyfold higher than those required to reduce plaque formation. However, RSV is an intracellular virus, and it is unknown whether plasma concentrations or respiratory secretion concentrations of the drug better reflect intracellular concentrations in the respiratory tract.

In man, rats, and rhesus monkeys, accumulation of ribavirin and/or metabolites in the red blood cells has been noted, plateauing in red cells in man in about 4 days and gradually declining with an apparent half-life of 40 days (the half-life of erythrocytes). The extent of accumulation of ribavirin following inhalation therapy is not well defined.

Animal Toxicology

Ribavirin, when administered orally or as an aerosol, produced cardiac lesions in mice, rats, and monkeys, when given at doses of 30, 36 and 120 mg/kg or greater for 4 weeks or more (estimated human equivalent doses of 4.8, 12.3 and 111.4 mg/kg for a 5 kg child, or 2.5, 5.1 and 40 mg/kg for a 60 kg adult, based on body surface area adjustment). Aerosolized ribavirin administered to developing ferrets at 60 mg/kg for 10 or 30 days resulted in inflammatory and possibly emphysematous changes in the lungs. Proliferative changes were seen in the lungs following exposure at 131 mg/kg for 30 days. The significance of these findings to human administration is unknown.

INDICATIONS AND USAGE

VIRAZOLE® (Ribavirin for Inhalation Solution, USP) is indicated for the treatment of hospitalized infants and young children with severe lower respiratory tract infections due to RSV. Treatment early in the course of severe lower respiratory tract infection may be necessary to achieve efficacy.

Only severe RSV lower respiratory tract infection should be treated with VIRAZOLE. The vast majority of infants and children with RSV infection have disease that is mild, self-limited, and does not require hospitalization or antiviral treatment. Many children with mild lower respiratory tract involvement will require shorter hospitalization than would be required for a full course of VIRAZOLE aerosol (3 to 7 days) and should not be treated with the drug. Thus the decision to treat with VIRAZOLE should be based on the severity of the RSV infection. The presence of an underlying condition such as prematurity, immunosuppression or cardiopulmonary disease may increase the severity of clinical manifestations and complications of RSV infection.

Use of aerosolized VIRAZOLE in patients requiring mechanical ventilator assistance should be undertaken only by physicians and support staff familiar with this mode of administration and the specific ventilator being used (see WARNINGS and DOSAGE AND ADMINISTRATION).

Diagnosis

RSV infection should be documented by a rapid diagnostic method such as demonstration of viral antigen in respiratory tract secretions by immunofluorescence^3,4 or ELISA^5 before or during the first 24 hours of treatment. Treatment may be initiated while awaiting rapid diagnostic test results. However, treatment should not be continued without documentation of RSV infection. Non-culture antigen detection techniques may have false positive or false negative results. Assessment of the clinical situation, the time of year and other parameters may warrant reevaluation of the laboratory diagnosis.

Description of Studies

Non-Mechanically Ventilated Infants: In two placebo-controlled trials in infants hospitalized with RSV lower respiratory tract infection, aerosolized VIRAZOLE treatment had a therapeutic effect, as judged by the reduction in severity of clinical manifestations of disease by treatment day 3.^3,4 Treatment was most effective when instituted within the first 3 days of clinical illness. Virus titers in respiratory secretions were also significantly reduced with VIRAZOLE in one of these original studies.^4 Additional controlled studies conducted since these initial trials of aerosolized VIRAZOLE in the treatment of RSV infection have supported these data.

Mechanically Ventilated Infants: A randomized, double-blind, placebo-controlled evaluation of aerosolized VIRAZOLE at the recommended dose was conducted in 28 infants requiring mechanical ventilation for respiratory failure caused by documented RSV infection.^6 Mean age was 1.4 months (SD, 1.7 months). Seven patients had underlying diseases predisposing them to severe infection and 21 were previously normal. Aerosolized VIRAZOLE treatment significantly decreased the duration of mechanical ventilation required (4.9 vs. 9.9 days, p=0.01) and duration of required supplemental oxygen (8.7 vs. 13.5 days, p=0.01). Intensive patient management and monitoring techniques were employed in this study. These included endotracheal tube suctioning every 1 to 2 hours; recording of proximal airway pressure, ventilatory rate, and FlO2 every hour; and arterial blood gas monitoring every 2 to 6 hours. To reduce the risk of VIRAZOLE precipitation and ventilator malfunction, heated wire tubing, two bacterial filters connected in series in the expiratory limb of the ventilator (with filter changes every 4 hours), and water column pressure release valves to monitor internal ventilator pressures were used in connecting ventilator circuits to the SPAG®-2.

Employing these techniques, no technical difficulties with VIRAZOLE administration were encountered during the study. Adverse events consisted of bacterial pneumonia in one case, staphylococcus bacteremia in one case and two cases of post-extubation stridor. None were felt to be related to VIRAZOLE administration.

CONTRAINDICATIONS

VIRAZOLE is contraindicated in individuals who have shown hypersensitivity to the drug or its components, and in women who are or may become pregnant during exposure to the drug. Ribavirin has demonstrated significant teratogenic and/or embryocidal potential in all animal species in which adequate studies have been conducted (rodents and rabbits). Therefore, although clinical studies have not been performed, it should be assumed that VIRAZOLE may cause fetal harm in humans. Studies in which the drug has been administered systemically demonstrate that ribavirin is concentrated in the red blood cells and persists for the life of the erythrocyte.

WARNINGS

SUDDEN DETERIORATION OF RESPIRATORY FUNCTION HAS BEEN ASSOCIATED WITH INITIATION OF AEROSOLIZED VIRAZOLE USE IN INFANTS. Respiratory function should be carefully monitored during treatment. If initiation of aerosolized VIRAZOLE treatment appears to produce sudden deterioration of respiratory function, treatment should be stopped and reinstituted only with extreme caution, continuous monitoring, and consideration of concomitant administration of bronchodilators.

Use with Mechanical Ventilators

USE OF AEROSOLIZED VIRAZOLE IN PATIENTS REQUIRING MECHANICAL VENTILATOR ASSISTANCE SHOULD BE UNDERTAKEN ONLY BY PHYSICIANS AND SUPPORT STAFF FAMILIAR WITH THIS MODE OF ADMINISTRATION AND THE SPECIFIC VENTILATOR BEING USED. Strict attention must be paid to procedures that have been shown to minimize the accumulation of drug precipitate, which can result in mechanical ventilator dysfunction and associated increased pulmonary pressures. These procedures include the use of bacteria filters in series in the expiratory limb of the ventilator circuit with frequent changes (every 4 hours), water column pressure release valves to indicate elevated ventilator pressures, frequent monitoring of these devices and verification that ribavirin crystals have not accumulated within the ventilator circuitry, and frequent suctioning and monitoring of the patient (see Description of Studies).

Those administering aerosolized VIRAZOLE in conjunction with mechanical ventilator use should be thoroughly familiar with detailed descriptions of these procedures as outlined in the SPAG-2 Instructions for Use.

PRECAUTIONS

General

Patients with severe lower respiratory tract infection due to RSV require optimum monitoring and attention to respiratory and fluid status (see SPAG-2 Instructions for Use).

Drug Interactions

Clinical studies of interactions of VIRAZOLE with other drugs commonly used to treat infants with RSV infections, such as digoxin, bronchodilators, other antiviral agents, antibiotics or anti-metabolites, have not been conducted. Interference by VIRAZOLE with laboratory tests has not been evaluated.

Carcinogenesis and Mutagenesis

Ribavirin increased the incidence of cell transformations and mutations in mouse Balb/c 3T3 (fibroblasts) and L5178Y (lymphoma) cells at concentrations of 0.015 and 0.03-5.0 mg/mL, respectively (without metabolic activation). Modest increases in mutation rates (3-4x) were observed at concentrations between 3.75-10.0 mg/mL in L5178Y cells in vitro with the addition of a metabolic activation fraction. In the mouse micronucleus assay, ribavirin was clastogenic at intravenous doses of 20-200 mg/kg, (estimated human equivalent of 1.67-16.7 mg/kg, based on body surface area adjustment for a 60 kg adult). Ribavirin was not mutagenic in a dominant lethal assay in rats at intraperitoneal doses between 50-200 mg/kg when administered for 5 days (estimated human equivalent of 7.14-28.6 mg/kg, based on body surface area adjustment; see Pharmacokinetics).

In vivo carcinogenicity studies with ribavirin are incomplete. However, results of a chronic feeding study with ribavirin in rats, at doses of 16-100 mg/kg/day (estimated human equivalent of 2.3-14.3 mg/kg/day, based on body surface area adjustment for the adult), suggest that ribavirin may induce benign mammary, pancreatic, pituitary and adrenal tumors. Preliminary results of two oral gavage oncogenicity studies in the mouse and rat (18-24 months; doses of 20-75 and 10-40 mg/kg/day, respectively [estimated human equivalent of 1.67-6.25 and 1.43-5.71 mg/kg/day, respectively, based on body surface area adjustment for the adult]) are inconclusive as to the carcinogenic potential of ribavirin (see Pharmacokinetics). However, these studies have demonstrated a relationship between chronic ribavirin exposure and increased incidences of vascular lesions (microscopic hemorrhages in mice) and retinal degeneration (in rats).

Impairment of Fertility

The fertility of ribavirin-treated animals (male or female) has not been fully investigated. However, in the mouse, administration of ribavirin at doses between 35-150 mg/kg/day (estimated human equivalent of 2.92-12.5 mg/kg/day, based on body surface area adjustment for the adult) resulted in significant seminiferous tubule atrophy, decreased sperm concentrations, and increased numbers of sperm with abnormal morphology. Partial recovery of sperm production was apparent 3-6 months following dose cessation. In several additional toxicology studies, ribavirin has been shown to cause testicular lesions (tubular atrophy) in adult rats at oral dose levels as low as 16 mg/kg/day (estimated human equivalent of 2.29 mg/kg/day, based on body surface area adjustment; see Pharmacokinetics). Lower doses were not tested. The reproductive capacity of treated male animals has not been studied.

PREGNANCY

Ribavirin has demonstrated significant teratogenic and/or embryocidal potential in all animal species in which adequate studies have been conducted. Teratogenic effects were evident after single oral doses of 2.5 mg/kg or greater in the hamster, and after daily oral doses of 0.3 and 1.0 mg/kg in the rabbit and rat, respectively (estimated human equivalent doses of 0.12 and 0.14 mg/kg, based on body surface area adjustment for the adult). Malformations of the skull, palate, eye, jaw, limbs, skeleton, and gastrointestinal tract were noted. The incidence and severity of teratogenic effects increased with escalation of the drug dose. Survival of fetuses and offspring was reduced. Ribavirin caused embryolethality in the rabbit at daily oral dose levels as low as 1 mg/kg. No teratogenic effects were evident in the rabbit and rat administered daily oral doses of 0.1 and 0.3 mg/kg, respectively with estimated human equivalent doses of 0.01 and 0.04 mg/kg, based on body surface area adjustment (see Pharmacokinetics). These doses are considered to define the No Observable Teratogenic Effects Level (NOTEL) for ribavirin in the rabbit and rat.

Following oral administration of ribavirin in the pregnant rat (1.0 mg/kg) and rabbit (0.3 mg/kg), mean plasma levels of drug ranged from 0.10-0.20 µM [0.024-0.049 µ/mL] at 1 hour after dosing, to undetectable levels at 24 hours. At 1 hour following the administration of 0.3 or 0.1 mg/kg in the rat and rabbit (NOTEL), respectively, mean plasma levels of drug in both species were near or below the limit of detection (0.05 µM; see Pharmacokinetics).

Although clinical studies have not been performed, VIRAZOLE may cause fetal harm in humans. As noted previously, ribavirin is concentrated in red blood cells and persists for the life of the cell. Thus the terminal half-life for the systemic elimination of ribavirin is essentially that of the half-life of circulating erythrocytes. The minimum interval following exposure to VIRAZOLE before pregnancy may be safely initiated is unknown (see CONTRAINDICATIONS, WARNINGS, and Information for Health Care Personnel).

Lactation

VIRAZOLE has been shown to be toxic to lactating animals and their offspring. It is not known if VIRAZOLE is excreted in human milk.

Information for Health Care Personnel

Health care workers directly providing care to patients receiving aerosolized VIRAZOLE should be aware that ribavirin has been shown to be teratogenic in all animal species in which adequate studies have been conducted (rodents and rabbits). Although no reports of teratogenesis in offspring of mothers who were exposed to aerosolized VIRAZOLE during pregnancy have been confirmed, no controlled studies have been conducted in pregnant women. Studies of environmental exposure in treatment settings have shown that the drug can disperse into the immediate bedside area during routine patient care activities with highest ambient levels closest to the patient and extremely low levels outside of the immediate bedside area. Adverse reactions resulting from actual occupational exposure in adults are described below (see Adverse Events in Health Care Workers). Some studies have documented ambient drug concentrations at the bedside that could potentially lead to systemic exposures above those considered safe for exposure during pregnancy (1/1000 of the NOTEL dose in the most sensitive animal species).^7,8,9

A 1992 study conducted by the National Institute of Occupational Safety and Health (NIOSH) demonstrated measurable urine levels of ribavirin in health care workers exposed to aerosol in the course of direct patient care.^7 Levels were lowest in workers caring for infants receiving aerosolized VIRAZOLE with mechanical ventilation and highest in those caring for patients being administered the drug via an oxygen tent or hood. This study employed a more sensitive assay to evaluate ribavirin levels in urine than was available for several previous studies of environmental exposure that failed to detect measurable ribavirin levels in exposed workers. Creatinine adjusted urine levels in the NIOSH study ranged from less than 0.001 to 0.140 µM of ribavirin per gram of creatinine in exposed workers. However, the relationship between urinary ribavirin levels in exposed workers, plasma levels in animal studies, and the specific risk of teratogenesis in exposed pregnant women is unknown.

It is good practice to avoid unnecessary occupational exposure to chemicals wherever possible. Hospitals are encouraged to conduct training programs to minimize potential occupational exposure to VIRAZOLE. Health care workers who are pregnant should consider avoiding direct care of patients receiving aerosolized VIRAZOLE. If close patient contact cannot be avoided, precautions to limit exposure should be taken. These include administration of VIRAZOLE in negative pressure rooms; adequate room ventilation (at least six air exchanges per hour); the use of scavenging devices; turning off the SPAG-2 device for 5 to 10 minutes prior to prolonged patient contact; and wearing appropriately fitted respirator masks. Surgical masks do not provide adequate filtration of VIRAZOLE particles. Further information is available from NIOSH’s Hazard Evaluation and Technical Assistance Branch and additional recommendations have been published in an Aerosol Consensus Statement by the American Respiratory Care Foundation and the American Association for Respiratory Care.^10

ADVERSE REACTIONS

The description of adverse reactions is based on events from clinical studies (approximately 200 patients) conducted prior to 1986, and the controlled trial of aerosolized VIRAZOLE conducted in 1989-1990. Additional data from spontaneous post-marketing reports of adverse events in individual patients have been available since 1986.

Deaths

Deaths during or shortly after treatment with aerosolized VIRAZOLE have been reported in 20 cases of patients treated with VIRAZOLE (12 of these patients were being treated for RSV infections). Several cases have been characterized as “possibly related” to VIRAZOLE by the treating physician; these were in infants who experienced worsening respiratory status related to bronchospasm while being treated with the drug. Several other cases have been attributed to mechanical ventilator malfunction in which VIRAZOLE precipitation within the ventilator apparatus led to excessively high pulmonary pressures and diminished oxygenation. In these cases the monitoring procedures described in the current package insert were not employed (see Description of Studies, WARNINGS, and DOSAGE AND ADMINISTRATION).

Pulmonary and Cardiovascular

Pulmonary function significantly deteriorated during aerosolized VIRAZOLE treatment in six of six adults with chronic obstructive lung disease and in four of six asthmatic adults. Dyspnea and chest soreness were also reported in the latter group. Minor abnormalities in pulmonary function were also seen in healthy adult volunteers.

In the original study population of approximately 200 infants who received aerosolized VIRAZOLE, several serious adverse events occurred in severely ill infants with life-threatening underlying diseases, many of whom required assisted ventilation. The role of VIRAZOLE in these events is indeterminate. Since the drug’s approval in 1986, additional reports of similar serious, though non-fatal, events have been filed infrequently. Events associated with aerosolized VIRAZOLE use have included the following:

Pulmonary: Worsening of respiratory status, bronchospasm, pulmonary edema, hypoventilation, cyanosis, dyspnea, bacterial pneumonia, pneumothorax, apnea, atelectasis and ventilator dependence.

Cardiovascular: Cardiac arrest, hypotension, bradycardia and digitalis toxicity. Bigeminy, bradycardia and tachycardia have been described in patients with underlying congenital heart disease.

Some subjects requiring assisted ventilation experienced serious difficulties, due to inadequate ventilation and gas exchange. Precipitation of drug within the ventilatory apparatus, including the endotracheal tube, has resulted in increased positive end expiratory pressure and increased positive inspiratory pressure. Accumulation of fluid in tubing (“rain out”) has also been noted. Measures to avoid these complications should be followed carefully (see DOSAGE AND ADMINISTRATION).

Hematologic

Although anemia was not reported with use of aerosolized VIRAZOLE in controlled clinical trials, most infants treated with the aerosol have not been evaluated 1 to 2 weeks post-treatment when anemia is likely to occur. Anemia has been shown to occur frequently with experimental oral and intravenous VIRAZOLE in humans. Also, cases of anemia (type unspecified), reticulocytosis and hemolytic anemia associated with aerosolized VIRAZOLE use have been reported through post-marketing reporting systems. All have been reversible with discontinuation of the drug.

Other

Rash and conjunctivitis have been associated with the use of aerosolized VIRAZOLE. These usually resolve within hours of discontinuing therapy. Seizures and asthenia associated with experimental intravenous VIRAZOLE therapy have also been reported.

Adverse Events in Health Care Workers

Studies of environmental exposure to aerosolized VIRAZOLE in health care workers administering care to patients receiving the drug have not detected adverse signs or symptoms related to exposure. However, 152 health care workers have reported experiencing adverse events through post-marketing surveillance. Nearly all were in individuals providing direct care to infants receiving aerosolized VIRAZOLE. Of 358 events from these 152 individual health care worker reports, the most common signs and symptoms were headache (51% of reports), conjunctivitis (32%), and rhinitis, nausea, rash, dizziness, pharyngitis, or lacrimation (10-20% each). Several cases of bronchospasm and/or chest pain were also reported, usually in individuals with known underlying reactive airway disease. Several case reports of damage to contact lenses after prolonged close exposure to aerosolized VIRAZOLE have also been reported. Most signs and symptoms reported as having occurred in exposed health care workers resolved within minutes to hours of discontinuing close exposure to aerosolized VIRAZOLE (also see Information for Health Care Personnel).

The symptoms of RSV in adults can include headache, conjunctivitis, sore throat and/or cough, fever, hoarseness, nasal congestion and wheezing, although RSV infections in adults are typically mild and transient. Such infections represent a potential hazard to uninfected hospital patients. It is unknown whether certain symptoms cited in reports from health care workers were due to exposure to the drug or infection with RSV. Hospitals should implement appropriate infection control procedures.

To report SUSPECTED ADVERSE REACTIONS, contact Bausch Health US, LLC at 1-800-321-4576 or FDA at 1-800-FDA-1088 or www.fda.gov/medwatch.

OVERDOSAGE

No overdosage with VIRAZOLE by aerosol administration has been reported in humans. The LD50 in mice is 2 g orally and is associated with hypoactivity and gastrointestinal symptoms (estimated human equivalent dose of 0.17 g/kg, based on body surface area conversion). The mean plasma half-life after administration of aerosolized VIRAZOLE for pediatric patients is 9.5 hours. VIRAZOLE is concentrated and persists in red blood cells for the life of the erythrocyte (see Pharmacokinetics).

DOSAGE AND ADMINISTRATION

BEFORE USE, READ THOROUGHLY THE BAUSCH HEALTH SMALL PARTICLE AEROSOL GENERATOR SPAG-2 INSTRUCTIONS FOR USE FOR SMALL PARTICLE AEROSOL GENERATOR OPERATING INSTRUCTIONS. AEROSOLIZED VIRAZOLE HAS NOT BEEN TESTED WITH ANY OTHER AEROSOL GENERATING DEVICE.

The recommended treatment regimen is 20 mg/mL VIRAZOLE as the starting solution in the drug reservoir of the SPAG-2 unit, with continuous aerosol administration for 12-18 hours per day for 3 to 7 days. Using the recommended drug concentration of 20 mg/mL the average aerosol concentration for a 12 hour delivery period would be 190 mcg/L of air. Aerosolized VIRAZOLE should not be administered in a mixture for combined aerosolization or simultaneously with other aerosolized medications.

Non-Mechanically Ventilated Infants

VIRAZOLE should be delivered to an infant oxygen hood from the SPAG®-2 aerosol generator. Administration by face mask or oxygen tent may be necessary if a hood cannot be employed (see SPAG-2 Instructions for Use). However, the volume and condensation area are larger in a tent and this may alter delivery dynamics of the drug.

Mechanically Ventilated Infants

The recommended dose and administration schedule for infants who require mechanical ventilation is the same as for those who do not. Either a pressure or volume cycle ventilator may be used in conjunction with the SPAG-2. In either case, patients should have their endotracheal tubes suctioned every 1-2 hours, and their pulmonary pressures monitored frequently (every 2-4 hours). For both pressure and volume ventilators, heated wire connective tubing and bacteria filters in series in the expiratory limb of the system (which must be changed frequently, i.e., every 4 hours) must be used to minimize the risk of VIRAZOLE precipitation in the system and the subsequent risk of ventilator dysfunction. Water column pressure release valves should be used in the ventilator circuit for pressure cycled ventilators, and may be utilized with volume cycled ventilators (see SPAG-2 INSTRUCTIONS FOR USE FOR DETAILED INSTRUCTIONS).

Method of Preparation

VIRAZOLE brand of ribavirin is supplied as 6 grams of lyophilized powder per 100 mL vial for aerosol administration only. By sterile technique, reconstitute drug with a minimum of 75 mL of Sterile Water for Injection, USP or Inhalation in the original 100 mL glass vial. Shake well. Transfer to the clean, sterilized 500 mL SPAG-2 reservoir and further dilute to a final volume of 300 mL with Sterile Water for Injection, USP or Inhalation. The final concentration should be 20 mg/mL. Important: This water should NOT have had any antimicrobial agent or other substance added. The solution should be inspected visually for particulate matter and discoloration prior to administration. Solutions that have been placed in the SPAG-2 unit should be discarded at least every 24 hours and when the liquid level is low before adding newly reconstituted solution.

HOW SUPPLIED

VIRAZOLE® (Ribavirin for Inhalation Solution, USP) is supplied in one-pack and four-pack counts containing 100 mL glass vials with 6 grams of Sterile, lyophilized drug, which is to be reconstituted with 300 mL Sterile Water for Injection, USP or Sterile Water for Inhalation (no preservatives added) and administered only by a small particle aerosol generator (SPAG®-2).

NDC 0187-0007-01 One 6 g glass vial
NDC 0187-0007-14 Four 6 g glass vials

Storage
Vials containing the lyophilized drug powder should be stored in a dry place at 25°C (77°F); excursions permitted to 15°C to 30°C (59°F to 86°F). Reconstituted solutions may be stored, under sterile conditions, at room temperature (20° to 30°C (68° to 86°F) for 24 hours. Solutions which have been placed in the SPAG-2 unit should be discarded at least every 24 hours.

REFERENCES

1. Hruska JF, Bernstein JM, Douglas Jr., RG, and Hall CB. Effects of Virazole on respiratory syncytial virus in vitro. Antimicrob Agents Chemother 17:770-775, 1980.
2. Hruska JF, Morrow PE, Suffin SC, and Douglas Jr., RG. In vivo inhibition of respiratory syncytial virus by Virazole. Antimicrob Agents Chemother 21:125-130, 1982.
3. Taber LH, Knight V, Gilbert BE, McClung HW et al. Virazole aerosol treatment of bronchiolitis associated with respiratory tract infection in infants. Pediatrics 72:613-618, 1983.
4. Hall CB, McBride JT, Walsh EE, Bell DM et al. Aerosolized Virazole treatment of infants with respiratory syncytial viral infection. N Engl J Med 308:1443-7, 1983.
5. Hendry RM, Mclntosh K, Fahnestock ML, and Pierik LT. Enzyme-linked immunosorbent assay for detection of respiratory syncytial virus infection J Clin Microbiol 16:329-33, 1982.
6. Smith, David W., Frankel, Lorry R., Mather, Larry H., Tang, Allen T.S., Ariagno, Ronald L., Prober, Charles G. A Controlled Trial of Aerosolized Ribavirin in Infants Receiving Mechanical Ventilation for Severe Respiratory Syncytial Virus Infection. N Engl J Med 1991; 325:24-29.
7. Decker, John, Shultz, Ruth A., Health Hazard Evaluation Report: Florida Hospital, Orlando, Florida. Cincinnati OH: U.S. Department of Health and Human Services, Public Health Service, Centers for NIOSH Report No. HETA 91-104-2229.*
8. Barnes, D.J. and Doursew, M. Reference dose: Description and use in health risk assessments. Regul Tox. and Pharm. Vol. 8; p. 471-486, 1988.
9. Federal Register Vol. 53 No. 126 Thurs. June 30, 1988 p. 24834-24847.
10. American Association for Respiratory Care [1991]. Aerosol Consensus Statement-1991. Respiratory Care 36(9): 916-921.

*Copies of the Report may be purchased from National Technical Information Service, 5285 Port Royal Road, Springfield, VA 22161; Ask for Publication PB 93119-345

Manufactured for:
Bausch Health US, LLC
Bridgewater, NJ 08807 USA

Manufactured by:
Hospira, Inc.
McPherson, KS 67460 USA
®/™ are trademarks of Bausch Health Companies Inc. or its affiliates.

© 2019 Bausch Health Companies Inc. or its affiliates
Rev. 05/2019
9680500
70014500

PRINCIPAL DISPLAY PANEL – 6 g Vial Carton

NDC 0187-0007-01

Rx only

Virazole®
(ribavirin for
inhalation
solution, USP)

6 grams

BAUSCH HEALTH

9680200